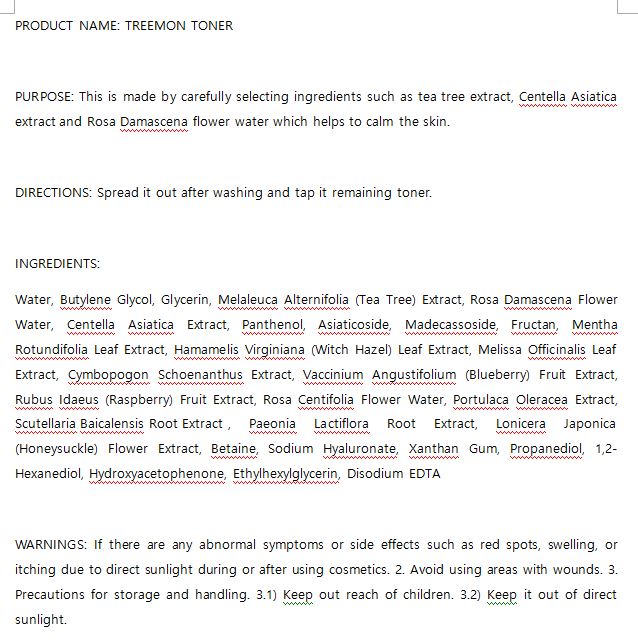 DRUG LABEL: W.SKIN TREEMON TONER
NDC: 74997-0023 | Form: LIQUID
Manufacturer: J&J COMPANY
Category: otc | Type: HUMAN OTC DRUG LABEL
Date: 20210508

ACTIVE INGREDIENTS: MELALEUCA ALTERNIFOLIA LEAF 1 g/100 mL
INACTIVE INGREDIENTS: GLYCERIN; WATER

J&J COMPANY - STOP-AGING PEPTIDE TONER

ACTIVE INGREDIENT

Melaleuca Alternifolia (Tea Tree) Extract

INACTIVE INGREDIENT

Water, Butylene Glycol, Glycerin, Melaleuca Alternifolia (Tea Tree) Extract, Rosa Damascena Flower Water, Centella Asiatica Extract, Panthenol, Asiaticoside, Madecassoside, Fructan, Mentha Rotundifolia Leaf Extract, Hamamelis Virginiana (Witch Hazel) Leaf Extract, Melissa Officinalis Leaf Extract, Cymbopogon Schoenanthus Extract, Vaccinium Angustifolium (Blueberry) Fruit Extract, Rubus Idaeus (Raspberry) Fruit Extract, Rosa Centifolia Flower Water, Portulaca Oleracea Extract, Scutellaria Baicalensis Root Extract , Paeonia Lactiflora Root Extract, Lonicera Japonica (Honeysuckle) Flower Extract, Betaine, Sodium Hyaluronate, Xanthan Gum, Propanediol, 1,2-Hexanediol, Hydroxyacetophenone, Ethylhexylglycerin, Disodium EDTA

PURPOSE

This is made by carefully selecting ingredients such as tea tree extract, Centella Asiatica extract and Rosa Damascena flower water which helps to calm the skin.

keep out of reach of the children

INDICATIONS AND USAGE

Spread it out after washing and tap it remaining toner

WARNINGS

If there are any abnormal symptoms or side effects such as red spots, swelling, or itching due to direct sunlight during or after using cosmetics. 2. Avoid using areas with wounds. 3. Precautions for storage and handling. 3.1) Keep out reach of children. 3.2) Keep it out of direct sunlight.

DOSAGE AND ADMINISTRATION

for external use only